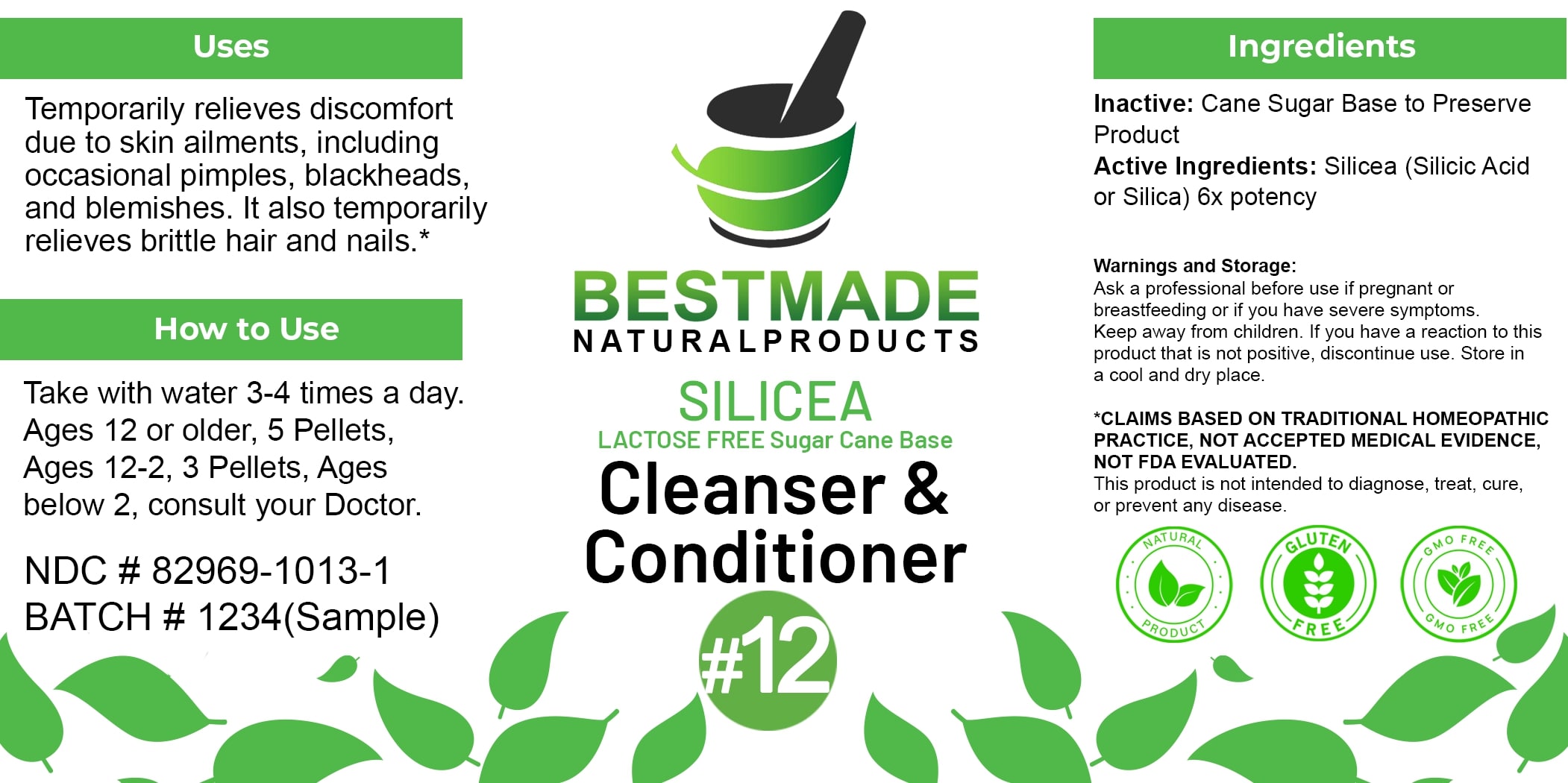 DRUG LABEL: Bestmade Natural Products Silicea 6x Lactose-free
NDC: 82969-1013 | Form: TABLET, SOLUBLE
Manufacturer: Bestmade Natural Products
Category: homeopathic | Type: HUMAN OTC DRUG LABEL
Date: 20250325

ACTIVE INGREDIENTS: SILICA 6 [hp_X]/6 [hp_X]
INACTIVE INGREDIENTS: SUCROSE 6 [hp_X]/6 [hp_X]

Silicea 6x Lactose-free

DOSAGE AND ADMINISTRATION

How to Use

Take with water 3-4 times a day. Ages 12 or older, 5 Pellets, Ages 12-2, 3 Pellets, Ages below 2, consult your Doctor.

Uses

Temporarily relieves discomfort due to skin ailments, including occasional pimples, blackheads, and blemishes. It also temporarily relieves brittle hair and nails.*

*CLAIMS BASED ON TRADITIONAL HOMEOPATHIC PRACTICE, NOT ACCEPTED MEDICAL EVIDENCE, NOT FDA EVALUATED. This product is not intended to diagnose, treat, cure, or prevent any disease.

INACTIVE INGREDIENT

Ingredients

Inactive: Cane Sugar Base to Preserve Product

ACTIVE INGREDIENT

Active Ingredients: Silicea (Silicic Acid or Silica) 6x potency

KEEP OUT OF REACH OF CHILDREN

Warnings and Storage:

Ask a professional before use if pregnant or breastfeeding or if you have severe symptoms. Keep away from children. If you have a reaction to this product that is not positive, discontinue use. Store in a cool and dry place.

Uses

Temporarily relieves discomfort due to skin ailments, including occasional pimples, blackheads, and blemishes. It also temporarily relieves brittle hair and nails.*

*CLAIMS BASED ON TRADITIONAL HOMEOPATHIC PRACTICE, NOT ACCEPTED MEDICAL EVIDENCE, NOT FDA EVALUATED. This product is not intended to diagnose, treat, cure, or prevent any disease.

Warnings and Storage:

Ask a professional before use if pregnant or breastfeeding or if you have severe symptoms. Keep away from children. If you have a reaction to this product that is not positive, discontinue use. Store in a cool and dry place.

*CLAIMS BASED ON TRADITIONAL HOMEOPATHIC PRACTICE, NOT ACCEPTED MEDICAL EVIDENCE, NOT FDA EVALUATED. This product is not intended to diagnose, treat, cure, or prevent any disease.

Entire package label.